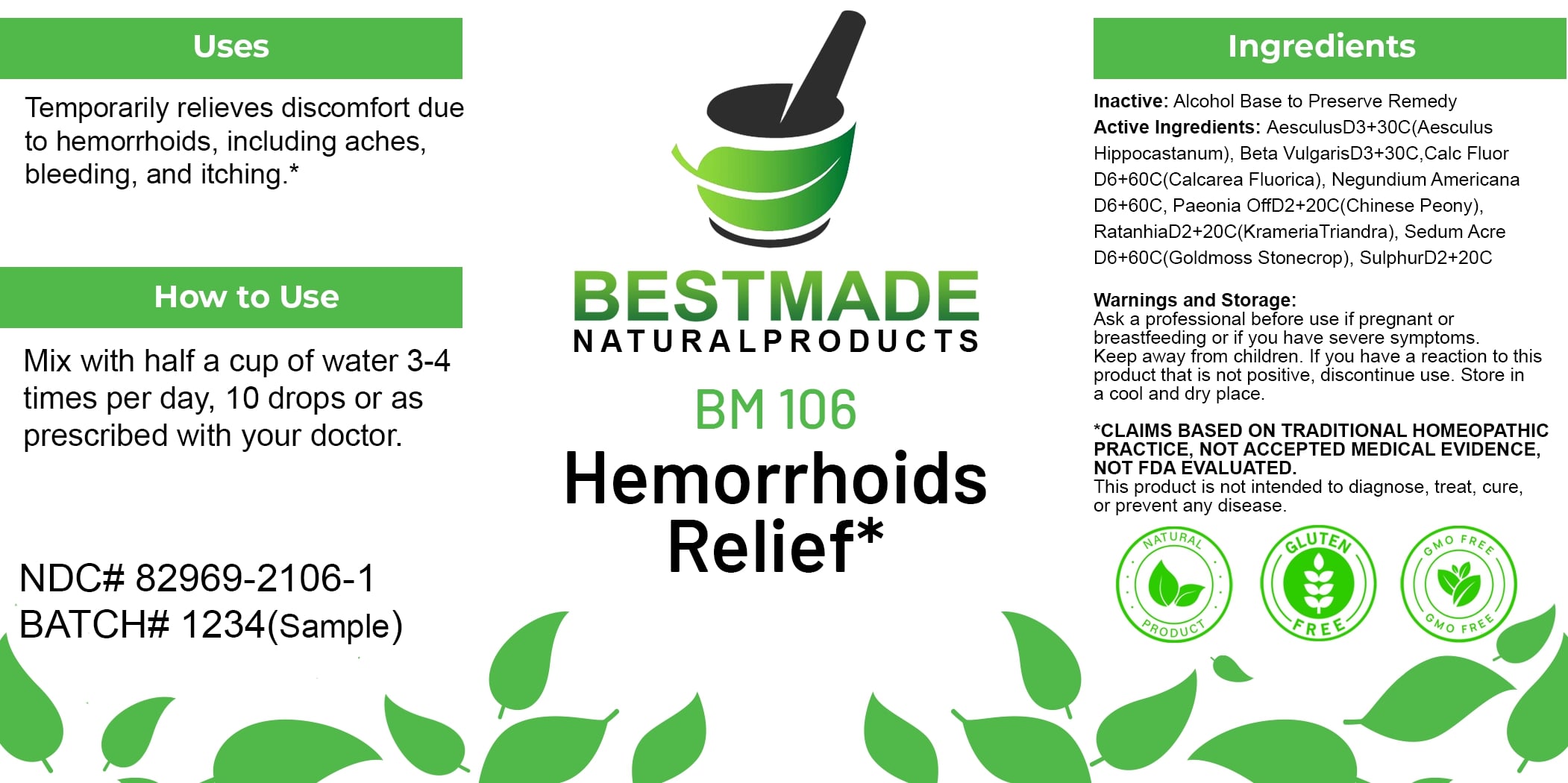 DRUG LABEL: Bestmade Natural Products BM106
NDC: 82969-2106 | Form: LIQUID
Manufacturer: Bestmade Natural Products
Category: homeopathic | Type: HUMAN OTC DRUG LABEL
Date: 20250207

ACTIVE INGREDIENTS: SULFUR 30 [hp_C]/30 [hp_C]; CALCIUM FLUORIDE 30 [hp_C]/30 [hp_C]; BETA VULGARIS 30 [hp_C]/30 [hp_C]; KRAMERIA LAPPACEA ROOT 30 [hp_C]/30 [hp_C]; ACER NEGUNDO WHOLE 30 [hp_C]/30 [hp_C]; HORSE CHESTNUT 30 [hp_C]/30 [hp_C]; PAEONIA OFFICINALIS ROOT 30 [hp_C]/30 [hp_C]; SEDUM ACRE 30 [hp_C]/30 [hp_C]
INACTIVE INGREDIENTS: ALCOHOL 30 [hp_C]/30 [hp_C]

BM106

DOSAGE AND ADMINISTRATION

How to Use

Mix with half a cup of water 3-4 times per day, 10 drops or as prescribed with your doctor.

INACTIVE INGREDIENT

Ingredients

Inactive: Alcohol Base to Preserve Remedy

ACTIVE INGREDIENT

Active Ingredients: AesculusD3+30C(Aesculus Hippocastanum), Beta VulgarisD3+30C, Calc Fluor D6+60C(Calcarea Fluorica), Negundium Americana D6+60C, Paeonia OffD2+20C(Chinese Peony), RatanhiaD2+20C(Krameria Triandra), Sedum Acre D6+60C(Goldmoss Stonecrop), SulphurD2+20C

KEEP OUT OF REACH OF CHILDREN

Warnings and Storage:

Ask a professional before use if pregnant or breastfeeding or if you have severe symptoms. Keep away from children. If you have a reaction to this product that is not positive, discontinue use. Store in a cool and dry place.

Warnings and Storage:

Ask a professional before use if pregnant or breastfeeding or if you have severe symptoms. Keep away from children. If you have a reaction to this product that is not positive, discontinue use. Store in a cool and dry place.

*CLAIMS BASED ON TRADITIONAL HOMEOPATHIC PRACTICE, NOT ACCEPTED MEDICAL EVIDENCE. NOT FDA EVALUATED. This product is not intended to diagnose, treat, cure, or prevent any disease.

Uses

Temporarily relieves discomfort due to hemorrhoids, including aches, bleeding, and itching.*

*CLAIMS BASED ON TRADITIONAL HOMEOPATHIC PRACTICE, NOT ACCEPTED MEDICAL EVIDENCE. NOT FDA EVALUATED. This product is not intended to diagnose, treat, cure, or prevent any disease.

Uses

Temporarily relieves discomfort due to hemorrhoids, including aches, bleeding, and itching.*

*CLAIMS BASED ON TRADITIONAL HOMEOPATHIC PRACTICE, NOT ACCEPTED MEDICAL EVIDENCE. NOT FDA EVALUATED. This product is not intended to diagnose, treat, cure, or prevent any disease.

Entire package label